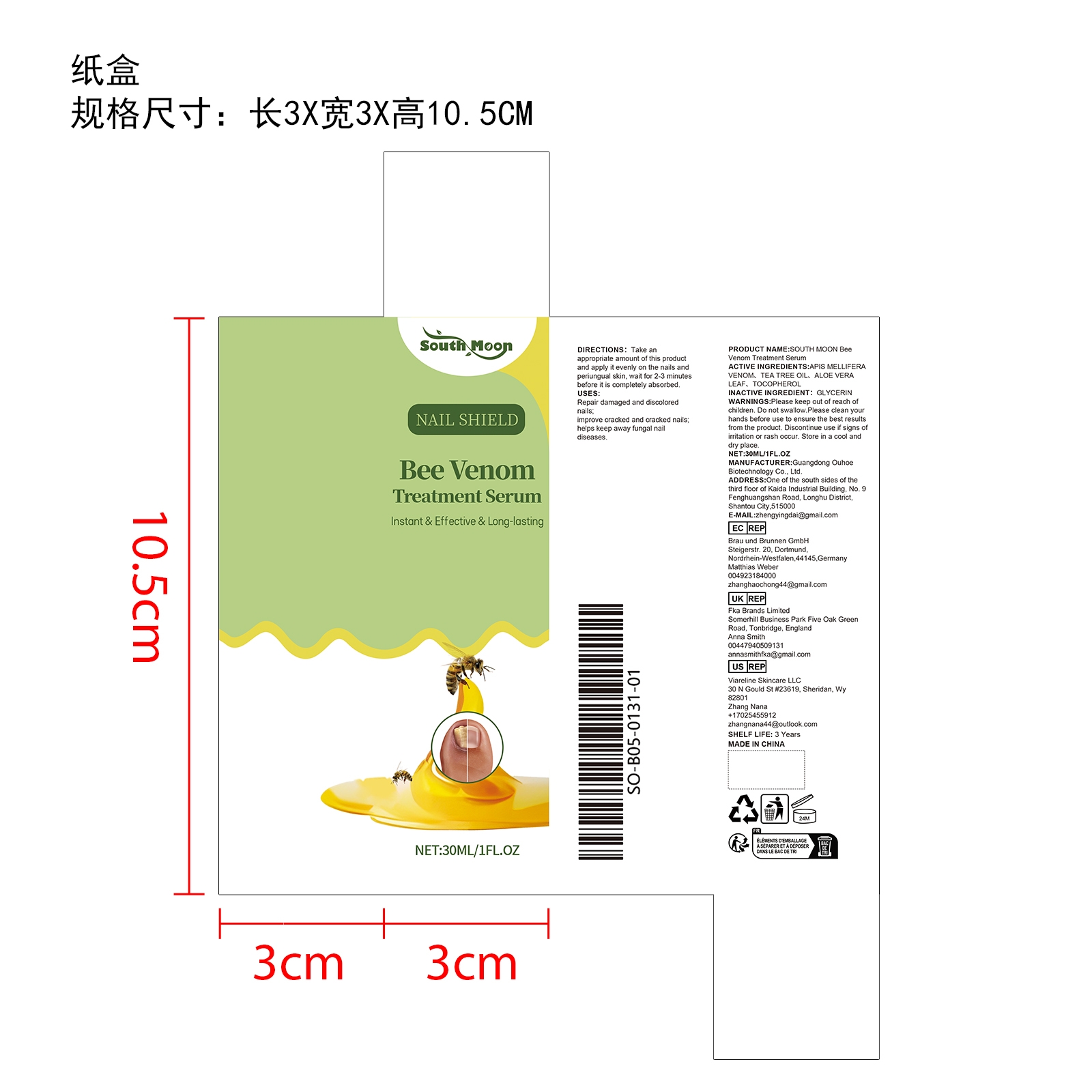 DRUG LABEL: SOUTH MOON Bee Venom Treatment Serum
NDC: 84744-011 | Form: LIQUID
Manufacturer: Guangdong Ouhoe Biotechnology Co., Ltd.
Category: otc | Type: HUMAN OTC DRUG LABEL
Date: 20241017

ACTIVE INGREDIENTS: APIS MELLIFERA VENOM 9 mg/30 mg; TOCOPHEROL 4.5 mg/30 mg; ALOE VERA LEAF 4.5 mg/30 mg; TEA TREE OIL 3 mg/30 mg
INACTIVE INGREDIENTS: GLYCERIN 9 mg/30 mg

ACTIVE INGREDIENTS

APIS MELLIFERA VENOM，
TEA TREE OIL,
ALOE VERA LEAF,
TOCOPHEROL

PURPOSE

Repair damaged and discolorednails;improve cracked and cracked nailshelps keep away fungal naildiseases.

USE

Take anappropriate amount of this product and apply it evenly on the nails and periungual skin, wait for 2-3 minutesbefore it is completely absorbed

WARNINGS

Please keep out of reach of children. Do not swallow.Please clean your hands before use to ensure the best results from the product. Discontinue use if signs of irritation or rash occur. Store in a cool and dry place.

DO NOT USE

Discontinue use if signs of irritation or rash occur.

STOP USE

Discontinue use if signs of irritation or rash occur.

Please keep out of reach of children.

STORAGE AND HANDLING

Store in a cool and dry place.

INACTIVE INGREDIENT

TOCOPHEROL